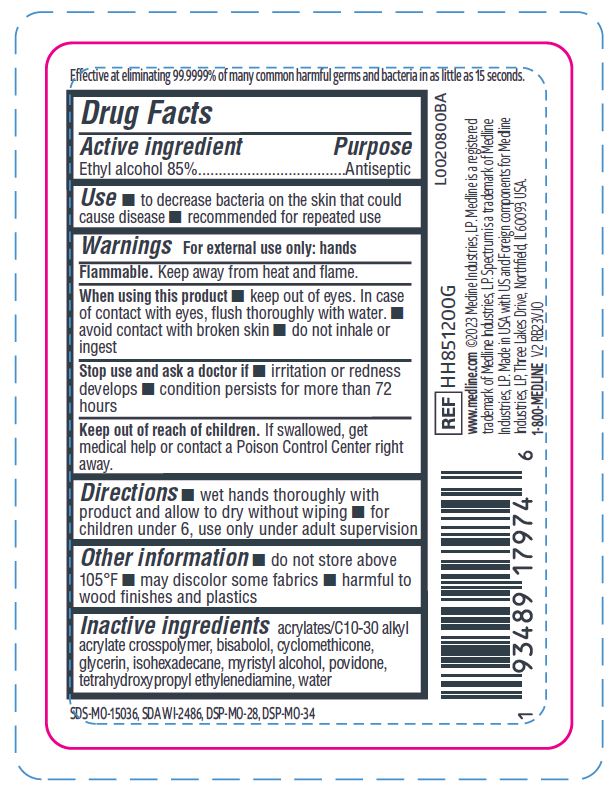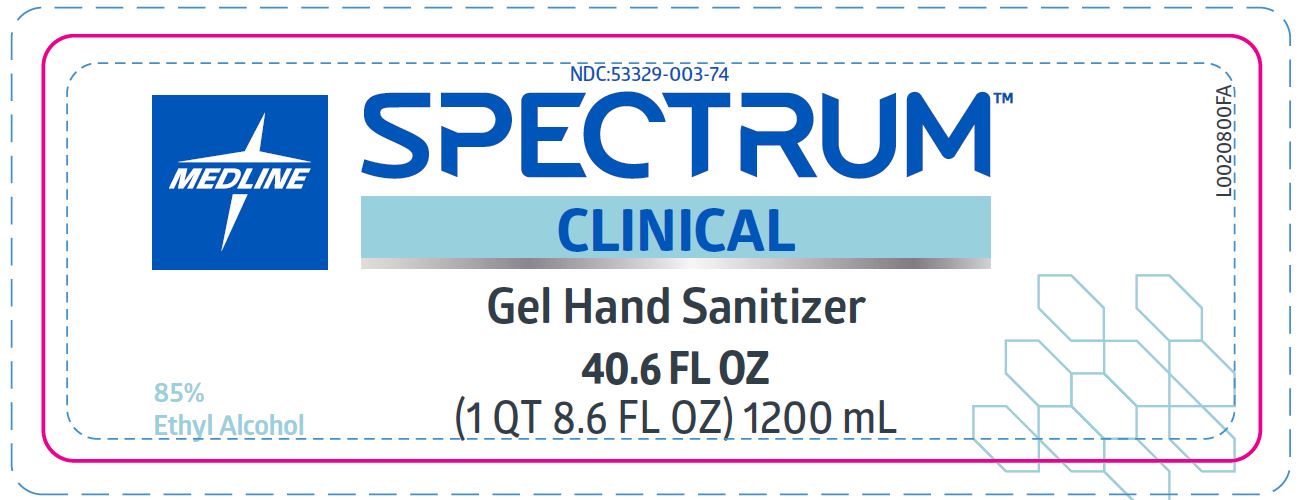 DRUG LABEL: Spectrum Hand Sanitizer
NDC: 53329-003 | Form: GEL
Manufacturer: Medline Industries, LP
Category: otc | Type: HUMAN OTC DRUG LABEL
Date: 20260211

ACTIVE INGREDIENTS: ALCOHOL 85 mL/100 mL
INACTIVE INGREDIENTS: LEVOMENOL; GLYCERIN; WATER; POVIDONE; MYRISTYL ALCOHOL; CYCLOMETHICONE; ISOHEXADECANE

003 Spectrum Clinical 85%

Active ingredient

Ethyl alcohol 85% v/v

Purpose

Antiseptic

Uses

- to decrease bacteria on the skin that could cause disease
- recommended for repeated use

Warnings

For external use only.

Flammable. Keep away from heat and flame.

When using this product

- keep out of eyes. In case of contact with eyes, flush thoroughly with water.
- avoid contact with broken skin
- do not inhale or ingest

Stop use and ask a doctor if

- irritation or redness develops
- condition persists for more than 72 hours

Keep out of reach of children.

If swallowed, get medical help or contact a Poison Control Center right away.

Directions

- wet hands thoroughly with product and allow to dry without wiping
- for children under 6, use only under adult supervision

Other information

- do not store above 105ºF
- may discolor some fabrics
- harmful to wood finishes and plastics

Inactive ingredients

acrylates/C10-30 alkyl acrylate crosspolymer, bisabolol, cyclomethicone, glycerin, isohexadecane, myristyl alcohol, povidone, tetrahydroxypropyl ethylenediamine, water

Manufacturing Information

Manufactured for:

Medline Industries, LP

Three Lakes Drive, Northfield, IL 60093 USA

Made in USA with US and Foreign components

www.medline.com

1-800-MEDLINE (633-5463)

REF: HH851200G

V2 RB23VJO